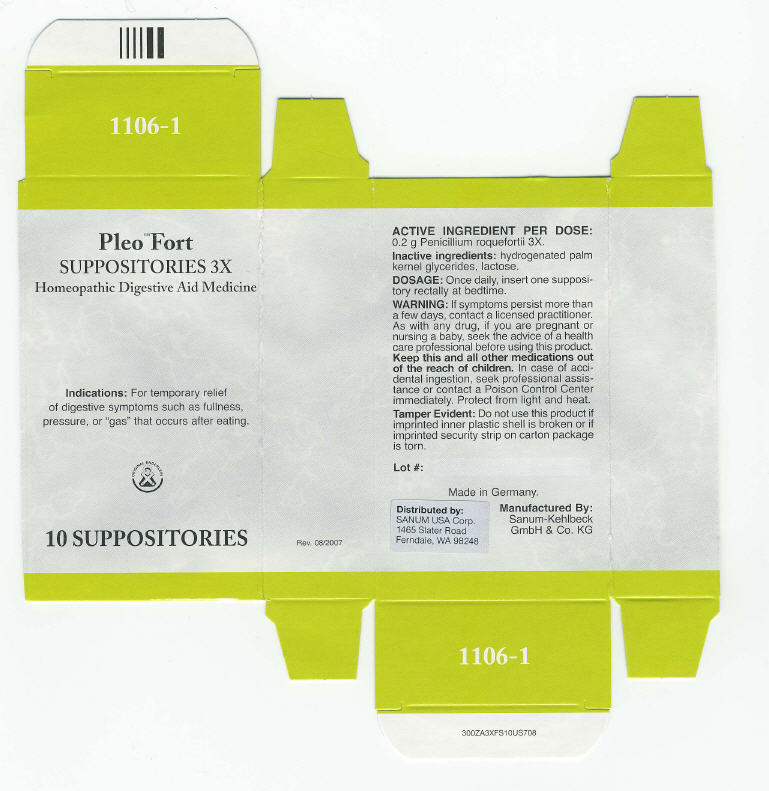 DRUG LABEL: Pleo Fort
NDC: 60681-1106 | Form: SUPPOSITORY
Manufacturer: Sanum Kehlbeck GmbH & Co. KG
Category: homeopathic | Type: HUMAN OTC DRUG LABEL
Date: 20091111

ACTIVE INGREDIENTS: penicillium roqueforti 3 [hp_X]/1 1
INACTIVE INGREDIENTS: lactose

Pleo™ Fort
SUPPOSITORIES 3X

Homeopathic Digestive Aid Medicine

10 SUPPOSITORIES

Indications

For temporary relief of digestive symptoms such as fullness, pressure, or "gas" that occurs after eating.

ACTIVE INGREDIENT PER DOSE

0.2 g Penicillium roquefortii 3X.

Inactive ingredients

hydrogenated palm kernel glycerides, lactose.

DOSAGE

Once daily, insert one suppository rectally at bedtime.

WARNING

If symptoms persist more than a few days, contact a licensed practitioner. As with any drug, if you are pregnant or nursing a baby, seek the advice of a health care professional before using this product.

KEEP OUT OF REACH OF CHILDREN

Keep this and all other medications out of the reach of children. In case of accidental ingestion, seek professional assistance or contact a Poison Control Center immediately.

STORAGE AND HANDLING

Protect from light and heat.

Tamper Evident

Do not use this product if imprinted inner plastic shell is broken or if imprinted security strip on carton package is torn.

Made in Germany.

Distributed by:
SANUM USA Corp.
1465 Slater Road
Ferndale, WA 98248

Manufactured By:
Sanum-Kehlbeck
GmbH & Co. KG

Rev. 08/2007

PRINCIPAL DISPLAY PANEL - 10 Suppository Carton

Pleo™ Fort
SUPPOSITORIES 3X

Homeopathic Digestive Aid Medicine

Indications: For temporary relief
of digestive symptoms such as fullness,
pressure, or "gas" that occurs after eating.

ORIGINAL ENDERLEIN

10 SUPPOSITORIES